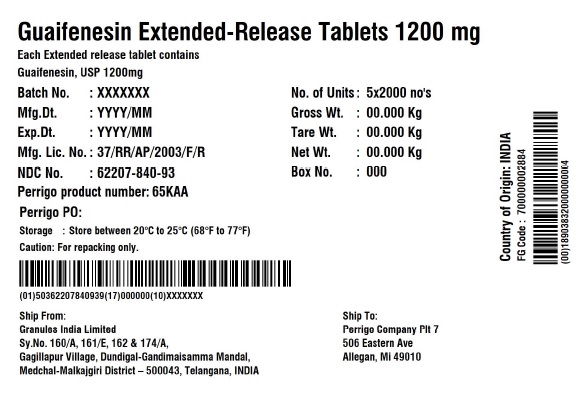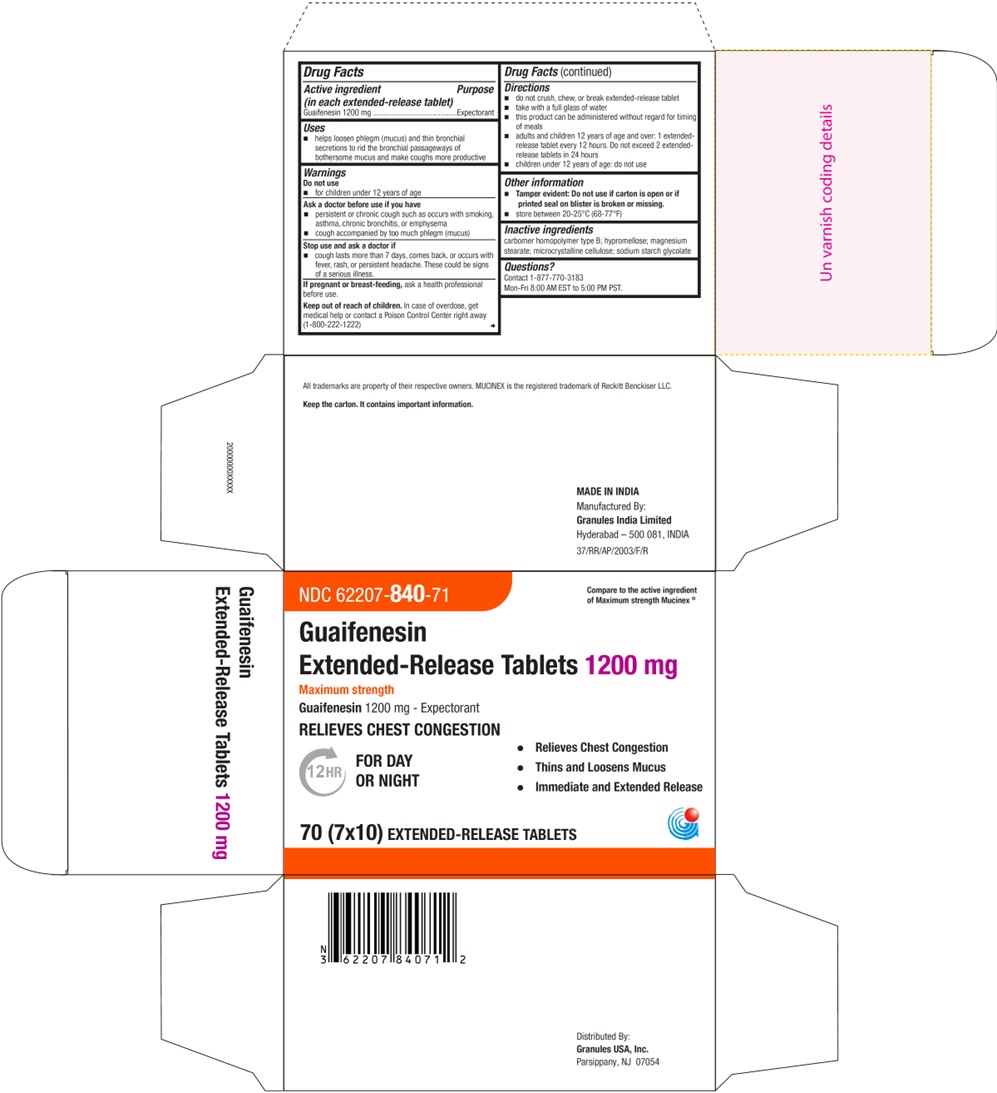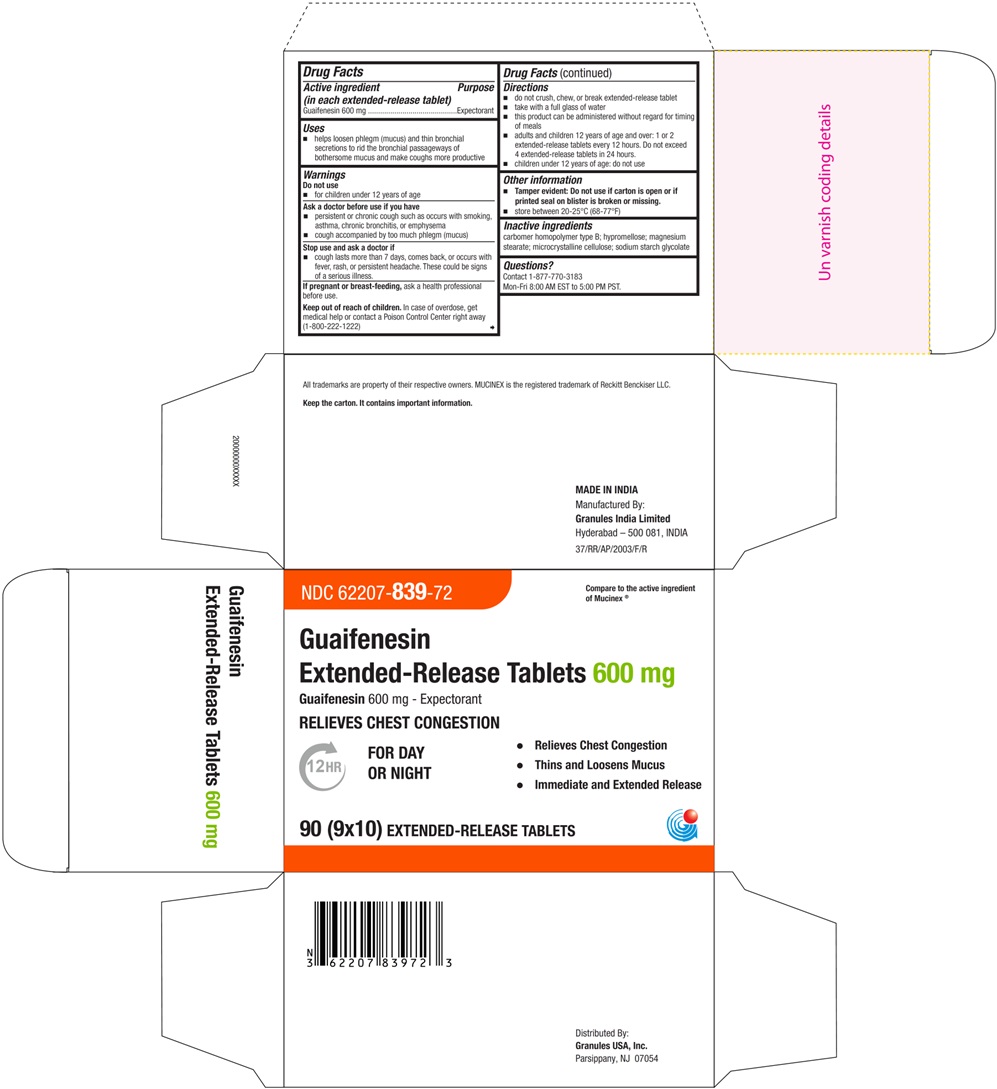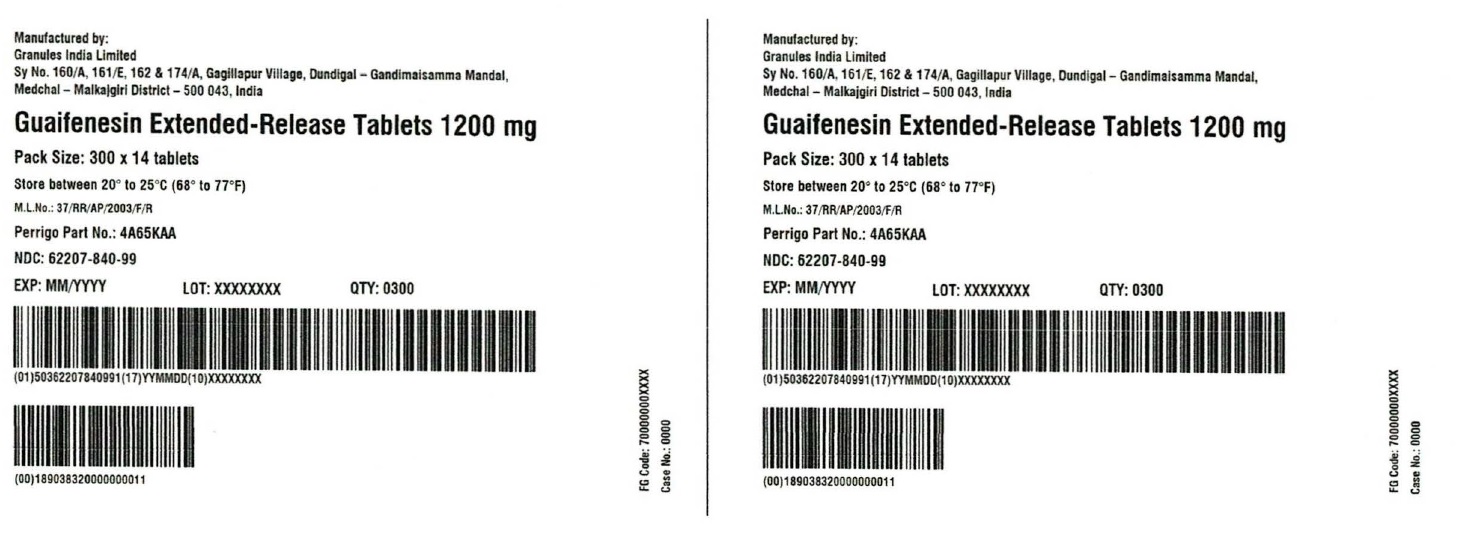 DRUG LABEL: GUAIFENESIN
NDC: 62207-839 | Form: TABLET, EXTENDED RELEASE
Manufacturer: Granules India Ltd
Category: otc | Type: HUMAN OTC DRUG LABEL
Date: 20251202

ACTIVE INGREDIENTS: GUAIFENESIN 600 mg/1 1
INACTIVE INGREDIENTS: HYPROMELLOSE 2910 (5 MPA.S); CARBOMER HOMOPOLYMER TYPE B (ALLYL SUCROSE CROSSLINKED); SODIUM STARCH GLYCOLATE TYPE A POTATO; MAGNESIUM STEARATE; MICROCRYSTALLINE CELLULOSE; HYPROMELLOSE 2910 (10000 MPA.S)

Guaifenesin Extended-Release Tablets, 600 mg and 1200 mg

Active ingredients (in each extended-release tablet)

Guaifenesin 600 mg (for 600 mg)

Guaifenesin 1200 mg (for 1200 mg)

purpose

Expectorant

Uses

- helps loosen phlegm (mucus) and thin bronchial secretions to rid the bronchial passageways of bothersome mucus and make coughs more productive

Warnings

Do not use

- for children under 12 years of age

Ask a doctor before use if you have

- persistent or chronic cough such as occurs with smoking, asthma, chronic bronchitis, or emphysema
- cough accompanied by too much phlegm (mucus)

Stop use and ask a doctor if

- cough lasts more than 7 days, comes back, or occurs with fever, rash, or persistent headache. These could be signs of a serious illness.

If pregnant or breast-feeding,

ask a health professional before use.

Keep out of reach of children

In case of overdose, get medical help or contact a Poison Control Center right away (1-800-222-1222)

Directions

- do not crush, chew, or break extended-release tablet
- take with a full glass of water
- this product can be administered without regard for timing of meals
- adults and children 12 years of age and over: 1 or 2 extended-release tablets every 12 hours. Do not exceed 4 extended-release tablets in 24 hours (For 600 mg)
- adults and children 12 years of age and over: 1 extended-release tablet every 12 hours. Do not exceed 2 extended-release tablets in 24 hours. (For 1200 mg)
- children under 12 years of age: do not use

Other information

- Tamper evident: Do not use if carton is open or if printed seal on blister is broken or missing.
- store between 20-25°C (68-77°F)

Inactive ingredients

carbomer homopolymer type B; hypromellose; magnesium stearate; microcrystalline cellulose; sodium starch glycolate

Questions?

Contact 1-877-770-3183
Mon-Fri 8:00 AM EST to 5:00 PM PST.

PRINCIPAL DISPLAY PANEL - 600 mg Blister Carton Label

NDC 62207- 839-72 Compare to the active ingredient
of Mucinex®

Guaifenesin
Extended-Release Tablets 600 mg

Guaifenesin 600 mg - Expectorant

RELIEVES CHEST CONGESTION

12HR FOR DAY • Relieves Chest Congestion
OR NIGHT • Thins and Loosens Mucus
• Immediate and Extended Release

90 (9 x 10) EXTENDED-RELEASE TABLETS

PRINCIPAL DISPLAY PANEL - 1200 mg Blister Carton Label

NDC 62207- 840-71 Compare to the active ingredient
of Mucinex®

Guaifenesin
Extended-Release Tablets 1200 mg

Maximum strength

Guaifenesin 1200 mg - Expectorant

RELIEVES CHEST CONGESTION

12HR FOR DAY • Relieves Chest Congestion
OR NIGHT • Thins and Loosens Mucus
• Immediate and Extended Release

70 (7 x 10) EXTENDED-RELEASE TABLETS